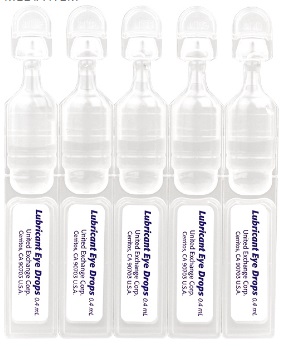 DRUG LABEL: Systane Ultra Single Vials
NDC: 65923-843 | Form: SOLUTION/ DROPS
Manufacturer: United Exchange Corp.
Category: otc | Type: HUMAN OTC DRUG LABEL
Date: 20180124

ACTIVE INGREDIENTS: PROPYLENE GLYCOL 3 mg/1 mL; POLYETHYLENE GLYCOL 400 4 mg/1 mL
INACTIVE INGREDIENTS: BORIC ACID; AMINOMETHYLPROPANOL; WATER; HYDROXYETHYL CELLULOSE (1800 MPA.S AT 2%); SODIUM CHLORIDE; SORBITOL; SODIUM HYDROXIDE; HYDROCHLORIC ACID; POTASSIUM CHLORIDE

Systane Ultra Single Eye Drops 0.4 ml 16843ZZ (2018)

Active ingredients Purpose

Polyethylene glycol 400 0.4%..............................Lubricant

Propylene glycol 0.3%.........................................Lubricant

Use

- for the temporary relief of burning and irritation due to dryness of the eye

Warnings

For external use only

Do not use

- if this product changes color or becomes cloudy
- if you are sensitive to any ingredient in this product

When using this product

- do not touch tip of container to any surface to avoid contamination
- do not reuse
- once opened, discard

Stop use and ask a doctor if

- you feel eye pain
- changes in vision occur
- redness or irritation of the eye(s) gets worse, persists or last more than 72 hours

Keep out of reach of children.

If swallowed, get medical help or contact a Poison Control Center right away

Directions

- Instill 1 or 2 drops in the affected eye(s) as needed.

Other information

- store at room temperature

Inactive ingredients

aminomethylpropanol, boric acid, hydrochloric acid, hydroxyethyl cellulose, potassium chloride, sodium hydroxide, sorbitol, water for injection

DOSAGE AND ADMINISTRATION

Made in South Korea